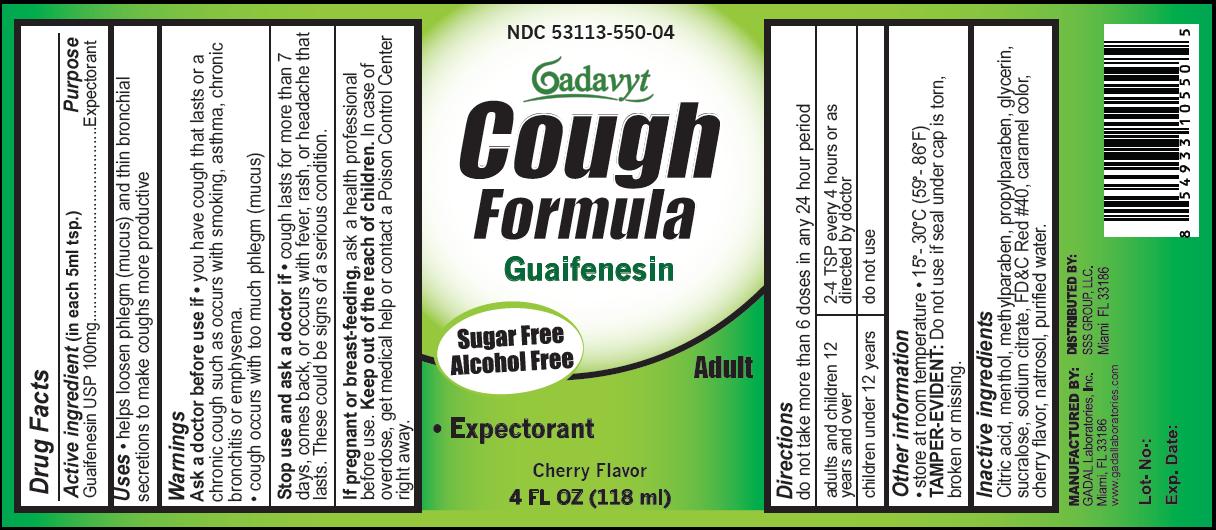 DRUG LABEL: Gadavyt Cough
NDC: 53113-550 | Form: LIQUID
Manufacturer: Gadal Laboratories Inc
Category: otc | Type: HUMAN OTC DRUG LABEL
Date: 20121217

ACTIVE INGREDIENTS: GUAIFENESIN 100 mg/5 mL
INACTIVE INGREDIENTS: CITRIC ACID MONOHYDRATE; MENTHOL; METHYLPARABEN; PROPYLPARABEN; GLYCERIN; SUCRALOSE; SODIUM CITRATE; FD&C RED NO. 40; HYDROXYETHYL CELLULOSE (2000 MPA.S AT 1%); WATER

Drug Facts

Active Ingredient (in each 5 mL tsp.) Purpose

Guaifenesin 100mg Expectorant

USES
Helps loosen phlegm (mucus) and thin bronchial
secretions to make coughs more productive

Warnings
Ask a doctor before use if

- you have cough that lasts or a chronic cough such as occurs with smoking, asthma, chronic bronchitis or emphysema.
- cough occurs with too much phlegm (mucus)

Stop use and ask a doctor if

- cough lasts for more than 7 days, comes back, or occurs with fever, rash, or headache that lasts. These could be signs of a serious condition.

KEEP OUT OF REACH OF CHILDREN

Keep out of the reach of children. In case of
overdose, get medical help or contact a Poison Control Center
right away.

PREGNANCY OR BREAST FEEDING

If pregnant or breast-feeding, ask a health professional
before use.

Directions

do not take more than 6 doses in any 24 hour period

adults and children 12 years and over | 2-4 TSP every 4 hours or as directed by doctor
children under 12 years | do not use

Other information
store at room temperature 15 - 30 degrees C (59 - 86 degrees F)
TAMPER-EVIDENT: Do not use if seal under cap is torn,
broken or missing.

Inactive Ingredients
Citric acid, menthol, methylparaben, propylparaben, glycerin,
sucralose, sodium citrate, FD and C Red No. 40, caramel color,
cherry flavor, natrosol, purified water.

QUESTIONS

GADAL Laboratories, Inc.

Miami, Fl 33186

www.gadallaboratories.com